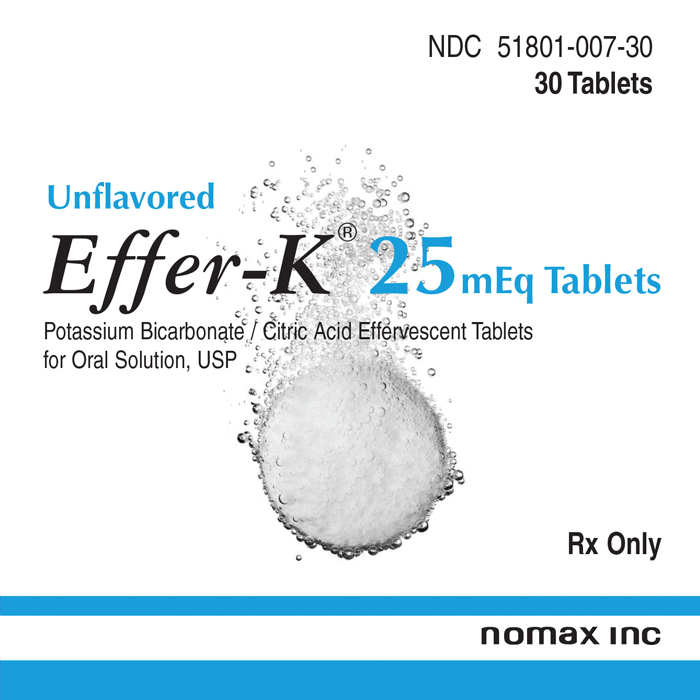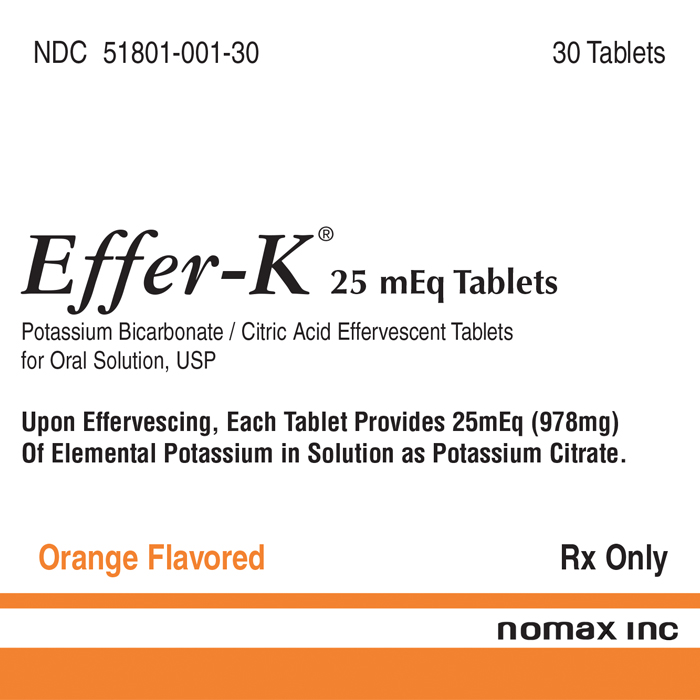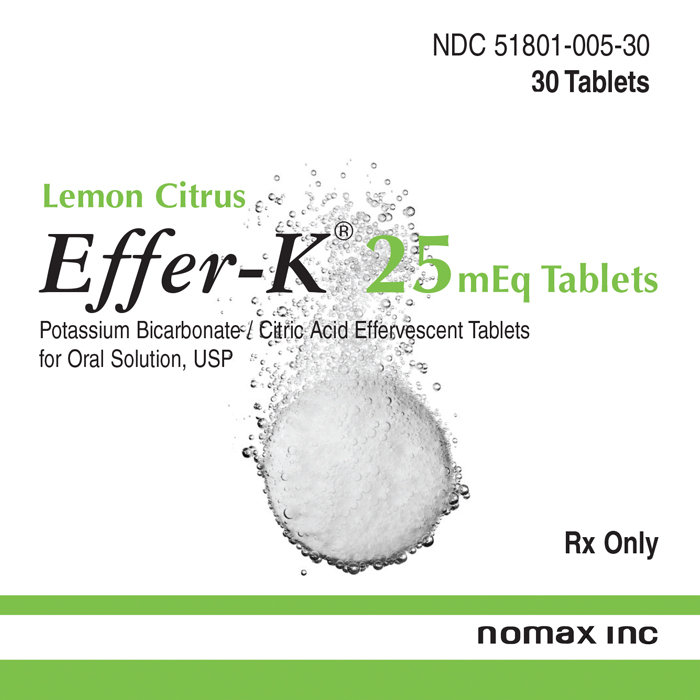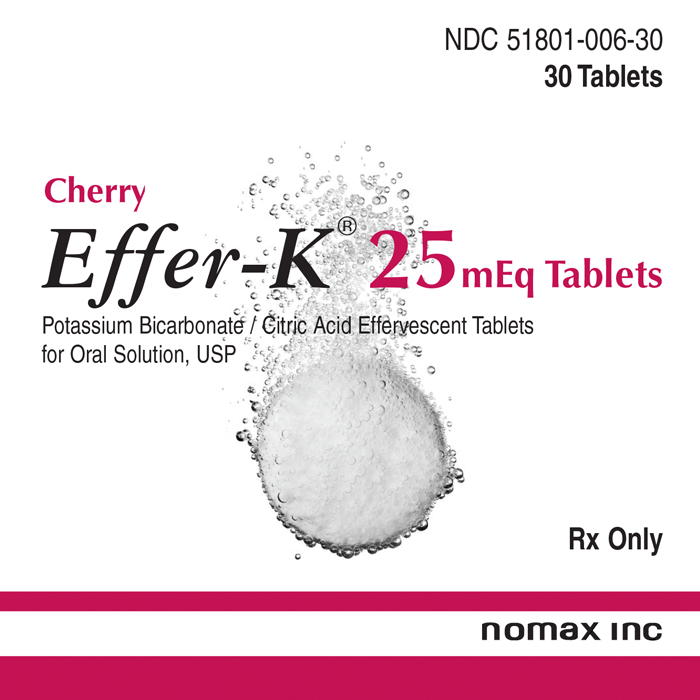 DRUG LABEL: Effer-K 
NDC: 51801-007 | Form: TABLET, EFFERVESCENT
Manufacturer: Nomax Inc.
Category: prescription | Type: HUMAN PRESCRIPTION DRUG LABEL
Date: 20191223

ACTIVE INGREDIENTS: POTASSIUM BICARBONATE 977.5 mg/1 1
INACTIVE INGREDIENTS: CITRIC ACID MONOHYDRATE 2100 mg/1 1; MINERAL OIL 34 mg/1 1; TALC 20 mg/1 1; CELLULOSE, MICROCRYSTALLINE 100 mg/1 1

Effer-K®
25 mEq

Description

Description: Effer-K® 25 mEq TABLETS (Potassium Bicarbonate Effervescent Tablets for Oral Solution, USP) are intended for the preparation of an oral solution of potassium. Each tablet contains 2.5 g. potassium bicarbonate and 2.1 g. citric acid which in solution provides 25 mEq (978 mg) of elemental potassium as potassium citrate. Tablets also contain: SD flavors, microcrystalline cellulose, mineral oil, saccharine and talc. The orange tablets contain FD&C yellow No. 6 and FD&C yellow No, 6 lake. The lemon citrus tablets contain D&C yellow No. 10 and yellow No. 10 lake. The cherry berry tablets contain FD&C red No. 40 and FD&C red No. 40 lake. The unflavored tablets do not contain any natural or synthetic dyes, flavors or sweeteners.

Tablets are one inch in diameter round, flat face on both sides with large bevels. "EK-25" is imprinted on one side of the tablets. Each tablet is foil-pouched with the product description on one side of the pouch and the lot number, expiration and barcode on the other.

Clinical Pharmacology

Potassium ion is the principal intracellular cation of most body tissues, whereas sodium ion is relatively low in concentration. In extracellular fluid the opposite exists, sodium ion being principal and potassium ion being low. The situation is maintained by an active membrane-bound enzyme (Na^+K^+ATPase). This potassium ion concentration gradient is essential to conduct nerve impulses in such specialized tissues as the brain, heart, and skeletal muscle; and in addition, to maintain normal renal function, acid-base balance, and various cellular metabolic functions. Elimination values are 90% renal and 10% fecal.

Potassium depletion may occur if the rate of potassium ion loss by renal excretion and/or loss from the gastrointestinal tract exceeds the rate of potassium ion intake. Such depletion usually develops slowly as a consequence of prolonged therapy with oral diuretics, primary or secondary hyperaldosteronism, diabetic ketoacidosis, severe diarrhea, or inadequate replacement of potassium in patients on prolonged parenteral nutrition. Potassium depletion due to these causes is usually accompanied by a concomitant deficiency of chloride and is manifested by hypokalemia and metabolic alkalosis. Potassium depletion may produce weakness, fatigue, mood or mental changes, nausea, vomiting, disturbances of cardiac rhythm (primarily ectopic beats), prominent U-waves in the electrocardiogram, and in advanced cases flaccid paralysis and/or impaired ability to concentrate urine.

Indications and Usage

1. For therapeutic use in patients with hypokalemia with or without metabolic alkalosis; in chronic digitalis intoxication; and in patients with hypokalemic familial periodic paralysis.
2. For prevention of potassium depletion when the dietary intake of potassium ion is inadequate in the following conditions; patients receiving digitalis and diuretics for congestive heart failure; hepatic cirrhosis with ascites; states of aldosterone excess with normal renal function; potassiumlosing nephropathy, and certain diarrheal states; long-term corticosteroid therapy.
3. The use of potassium salts in patients receiving diuretics for uncomplicated essential hypertension or receiving certain antibiotics is often unnecessary when such patients have a normal dietary pattern. Serum potassium should be checked periodically, however, and, if hypokalemia occurs, dietary supplementation with potassium-containing foods may be adequate to control milder cases. In more severe cases supplementation with potassium salts may be indicated.

Contraindications

Potassium supplements are contraindicated in patients with hyperkalemia since a further increase in serum potassium concentration in such patients can produce cardiac arrest. Conditions predisposing to hyperkalemia include: chronic renal failure, acute metabolic acidosis, uncontrolled diabetes mellitus, esophageal compression or delayed gastric emptying or intestinal obstruction/stricture or peptic ulcer. Potassium supplements should be used with caution and only where medically indicated in patients with familial periodic paralysis, myotonia congenita or severe/complete heart block. IMPORTANT: Potassium supplements are contraindicated in patients receiving potassium-sparing diuretics (e.g. spironolactone, triamterene) since such use may produce severe hyperkalemia.

Warnings

In patients with hyperkalemia and impaired mechanisms for excreting potassium the administration of potassium salts can produce hyperkalemia and cardiac arrest. This occurs most commonly in patients given potassium by the intravenous route but may also occur in patients given potassium orally. Potentially fatal hyperkalemia can develop rapidly and be asymptomatic.

The use of potassium salts in patients with chronic renal disease, or any other condition which impairs potassium excretion, requires particularly careful monitoring of the serum potassium concentration and appropriate dosage adjustment.

Note: There is no conclusive evidence that potassium supplements lower blood pressure in hypertensive patients.

Precautions

The diagnosis of potassium depletion is ordinarily made by demonstrating hypokalemia in a patient with a clinical history suggesting some cause for potassium depletion. In interpreting the serum potassium level, the physician should bear in mind that acute alkalosis per se can produce hypokalemia in the absence of a deficit in total body potassium, while acute acidosis per se can increase the serum potassium concentration into the normal range even in the presence of a reduced total body potassium. The treatment of potassium depletion, particularly in the presence of cardiac disease, renal disease, or acidosis, requires careful attention to acid-base balance and appropriate monitoring of serum electrolytes, the electrocardiogram, and the clinical status of the patient.

Information for patients

To minimize the possibility of gastrointestinal irritation associated with the oral ingestion of concentrated potassium salt preparations, patients should be directed to dissolve each dose completely in the stated amount of water.

Each dose should be taken immediately after a meal or with food. Patients should avoid low-salt foods and salt substitutes, unless approved by physician. The patient should be cautioned to comply strictly with the regimen, particularly when taking diuretics or digitalis, to visit the physician regularly and to report at once any unusual symptoms (e.g. blackish stools, a sign of gastrointestinal bleeding). As with any other medicine, the patient should be counseled on this background information and advised to report to the physician any changes in routine (e.g. starting a fitness program). Proper storage and handling of the product is important. Tablets should not be removed from foil pouch until shortly before use.

Laboratory tests

Frequent clinical evaluation of the patient should include an ECG and a serum potassium level; also, as appropriate, renal function, serum magnesium and serum pH.

Drug Interactions

The simultaneous administration of potassium supplements and a potassium-sparing diuretic can produce severe hyperkalemia (see Contraindications). Potassium supplements should be used cautiously in patients who are using salt substitutes, because most of the latter contain substantial amounts of potassium. Such concomitant use could result in hyperkalemia.

Moreover, the following drugs may produce unfavorable interactions when used concomitantly with potassium supplements: angiotension-converting enzyme (ACE) inhibitors, nonsteroid anti-inflammatory drugs (NSAIDs), beta-adrenergic blocking drugs, heparin, low-salt foods, other potassium containing medications, digitalis glycosides and others.

Carcinogenesis, Mutagenesis, Impairment of Fertility

Potassium is an essential constituent of the human diet. There are no data available on long-term potential for carcinogenicity, mutagenicity, or impairment of fertility in animals or in human beings.

Usage in Pregnancy

Pregnancy Category C

Animal reproduction studies have not been conducted with Effer-K® 25mEq TABLETS (Potassium Bicarbonate Effervescent Tablets for Oral Solution, USP). It is also not known whether these products can cause fetal harm when administered to a pregnant woman or can affect reproduction capacity. Effer-K® 25mEq TABLETS (Potassium Bicarbonate Effervescent Tablets for Oral Solution, USP) should be given to a pregnant woman only if clearly needed.

Labor and Delivery

Information unknown.

Nursing Mothers

Although no studies have been done, it is presumed that potassium is excreted in human milk. Caution should be exercised when Effer-K® 25mEq TABLETS (Potassium Bicarbonate Effervescent Tablets for Oral Solution, USP) are administered to a nursing woman.

Usage in Children

Safety and effectiveness in children have not been established.

Adverse Reactions

One of the most severe adverse effects is hyperkalemia (see Contraindications, Warnings and Overdosage). The most common adverse reactions to oral potassium salts are nausea, vomiting, abdominal discomfort, and diarrhea. These symptoms are due to irritation of the gastrointestinal tract and are best managed by diluting the preparation further, taking the dose with meals, or reducing the dose. Skin rash has been reported rarely.

Overdosage

The administration of oral potassium salts to persons with normal excretory mechanisms for potassium rarely causes serious hyperkalemia. However, if excretory mechanisms are impaired or if potassium is administered too rapidly intravenously, potentially fatal hyperkalemia can result (see Contraindications and Warnings). It is important to recognize that initally hyperkalemia is usually asymptomatic and may be manifested only by an increased serum potassium concentration and characteristic electrocardiographic changes (peaking of T-waves, loss of P-wave, depression of S-T segment, and prolongation of the QT interval). Late manifestations include muscle paralysis and cardiovascular collapse from cardiac arrest.

Treatment measures for hyperkalemia include the elimination of foods and medications containing potassium and potassium-sparing diuretics, as well as ACE inhibitors, beta blocking agents, NSAIDs, heparin, and cyclosporine. In cases of life-threatening hyperkalemia, treatment measures may include: (1) intravenous administration of 300 to 500 ml/hr of 10% dextrose solution containing 10-20 units of insulin per 1,000 ml; (2) correction of acidosis, if present, with intravenous sodium bicarbonate; (3) use of exchange resins, hemodialysis, or peritoneal dialysis; (4) administration of a calcium salt to antagonize the cardiotoxic effects in patients whose electrocardiograms show appropriate characteristics, and who are not receiving digitalis glycosides; and (5) maintenance of a high urine output in suitable patients.

In treating hyperkalemia, it should be recalled that in patients who have been stabilized on digitalis, rapid lowering of serum potassium can produce digitalis toxicity.

Dosage and Administration: Adults- One Effer-K® flavored tablet, (Orange, Lemon Citrus or Cherry Berry) each containing 25 mEq (978 mg) of potassium, completely dissolved in 4 ounces of cold or ice water, 1 to 4 times daily, depending on the requirement of the patient. For Effer-K® unflavored tablets (each containing 25 mEq (978 mg) of potassium) we recommend completely dissolving one tablet in 12 to 16 ounces of cold juice of the patient's choice.

NOTE: It is suggested that any effervescent potassium tablets be taken with meals and sipped slowly over a 5 to 10 minute period.

How Supplied

STORAGE AND HANDLING

Effer-K® 25 mEq TABLETS (Potassium Bicarbonate Effervescent Tablets for Oral Solution, USP). Each tablet in solution provides 25 mEq of elemental potassium as potassium citrate. Store below 40˚C (104˚F) preferably between 15˚ and 30˚C (59˚ and 86˚F), in original hermetic packaging.

Tablets are one inch diameter round, flat face on both sides with large bevels. "EK 25" is imprinted one side of the tablets. Each tablet is pouched with the product description on one side of the pouch and the lot number, expiration date, and barcode on the other.

NDC 51801-001-30 Orange-flavored, package of 30 tablets. | NDC 51801-005-30 Lemon Citrus-flavored, package of 30 tablets.
NDC 51801-001-40 Orange-flavored, package of 100 tablets. | NDC 51801-006-30 Cherry Berry-flavored, package of 30 tablets.
 | NDC 51801-007-30 Unflavored, package of 30 tablets.

Nomax, Inc. St. Louis, MO 63123 - Made in USA
MSN 015-031

Rev. 08/10

PRINCIPAL DISPLAY PANEL - 30 Tablet Pouch Carton - Unflavored

NDC 51801-007-30
30 Tablets

Effer-K® 25 mEq Tablets

POTASSIUM BICARBONATE EFFERVESCENT TABLETS
FOR ORAL SOLUTION, USP

Each Tablet contains 25mEq (978 mg) of Potassium

Unflavored (Dissolve in 12-16 ounces of juice)
Rx Only

nomax inc

PRINCIPAL DISPLAY PANEL - 30 Tablet Pouch Carton - Orange

NDC 51801-001-30
30 Tablets

Effer-K® 25 mEq Tablets

POTASSIUM BICARBONATE EFFERVESCENT TABLETS
FOR ORAL SOLUTION, USP

Each Tablet contains 25mEq (978 mg) of Potassium

Orange Flavored
Rx Only

nomax inc

PRINCIPAL DISPLAY PANEL - 30 Tablet Pouch Carton - Lemon

NDC 51801-005-30
30 Tablets

Effer-K® 25 mEq Tablets

POTASSIUM BICARBONATE EFFERVESCENT TABLETS
FOR ORAL SOLUTION, USP

Each Tablet contains 25mEq (978 mg) of Potassium

Lemon Citrus Flavored
Rx Only

nomax inc

PRINCIPAL DISPLAY PANEL - 30 Tablet Pouch Carton - Cherry

NDC 51801-006-30
30 Tablets

Effer-K® 25 mEq Tablets

POTASSIUM BICARBONATE EFFERVESCENT TABLETS
FOR ORAL SOLUTION, USP

Each Tablet contains 25mEq (978 mg) of Potassium

Cherry Berry Flavored
Rx Only

nomax inc